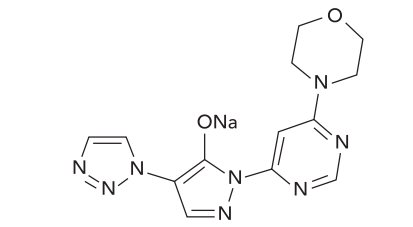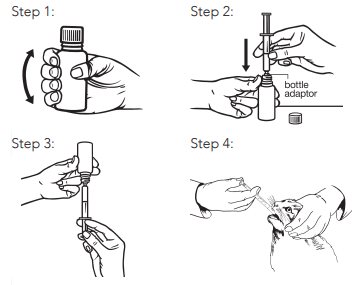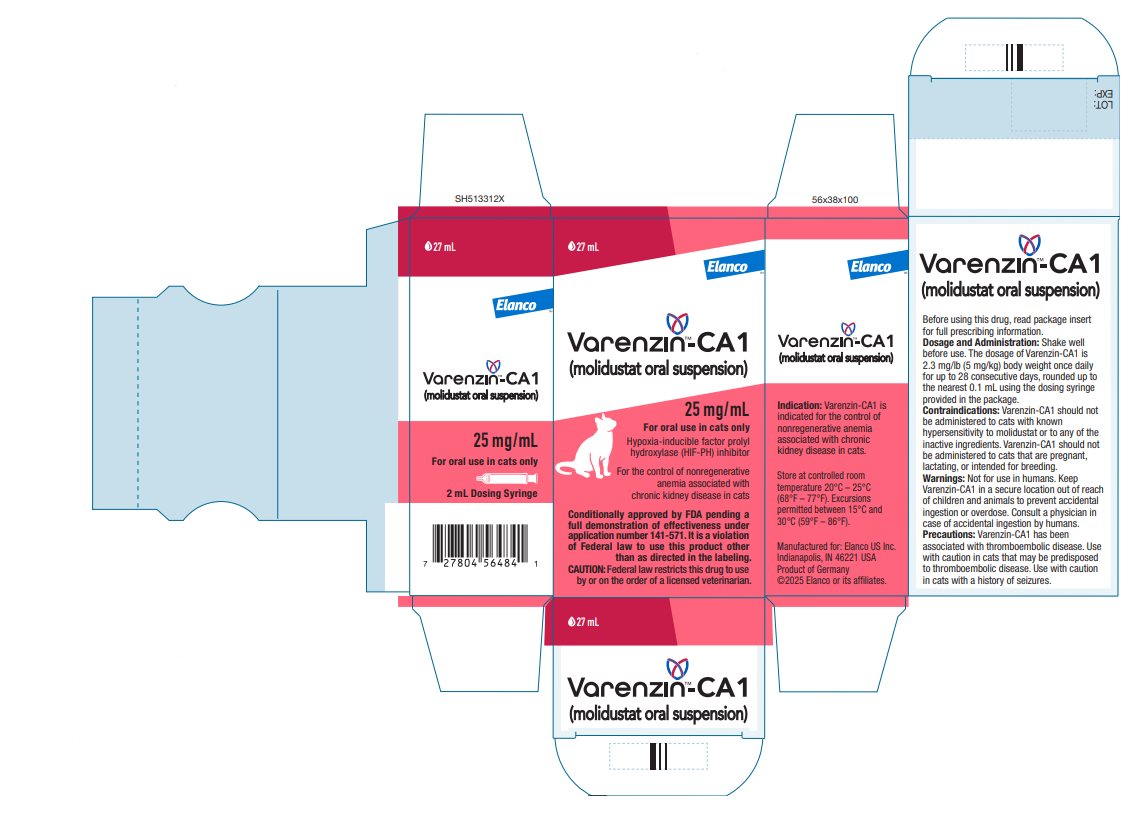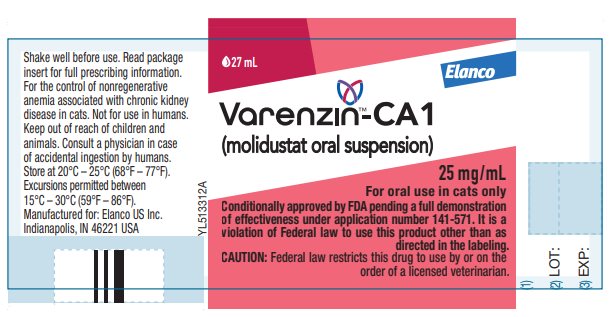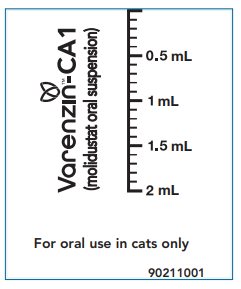 DRUG LABEL: Varenzin-CA1
NDC: 58198-3697 | Form: SUSPENSION
Manufacturer: Elanco US Inc.
Category: animal | Type: PRESCRIPTION ANIMAL DRUG LABEL
Date: 20250721

ACTIVE INGREDIENTS: MOLIDUSTAT SODIUM 25 mg/1 mL

ElancoTM

Varenzin™-CA1

(molidustat oral suspension)

Hypoxia-inducible factor prolyl hydroxylase (HIF-PH) inhibitor

25 mg/mL

For oral use in cats only

Conditionally approved by FDA pending a full demonstration of effectiveness under application number 141-571. It is a violation of Federal law to use this product other than as directed in the labeling.

CAUTION:

Federal law restricts this drug to use by or on the order of a licensed veterinarian.

DESCRIPTION

Varenzin-CA1 (molidustat oral suspension) is a white to yellow-white oily suspension. Each mL of Varenzin-CA1 contains 25 mg of molidustat sodium. The inactive ingredients are glycerol dibehenate, fish oil, sunflower oil, butylhydroxytoluene, and sorbic acid. The empirical formula is C13H13N8O2Na and the molecular weight is 336.28. The chemical name is Sodium 1-[6-(morpholin-4-yl)pyrimidin-4-yl]-4-(1H-1,2,3-triazol-1-yl)-1H-pyrazol-5-olate. The chemical structure of molidustat sodium is:

INDICATION

Varenzin-CA1 is indicated for the control of nonregenerative anemia associated with chronic kidney disease (CKD) in cats.

DOSAGE AND ADMINISTRATION

Shake well before use.

The dosage of Varenzin-CA1 is 2.3 mg/lb (5 mg/kg) body weight (bw) administered orally once daily for up to 28 consecutive days. Treatment may be repeated after a minimum 7-day pause (see Monitoring and Repeating Treatment). Varenzin-CA1 should be administered using the dosing syringe provided in the package. The dosing syringe is marked in increments of 0.1 mL. The dose should be rounded up to the nearest 0.1 mL.

Dosing Information

To ensure the correct dose is administered, body weight should be determined prior to starting each treatment cycle.

Table 1. Dosing Chart

Weight Range in; pounds (lb) | Volume of; Varenzin-CA1 (mL)
3.4 to 4.4 | 0.4
4.5 to 5.5 | 0.5
5.6 to 6.6 | 0.6
6.7 to 7.7 | 0.7
7.8 to 8.8 | 0.8
8.9 to 9.9 | 0.9
10 to 11 | 1
11.1 to 12.1 | 1.1
12.2 to 13.2 | 1.2

Note: The syringe included with the Varenzin-CA1 product cannot be used to accurately dose cats weighing under 3.4 pounds. Cats greater than 13.2 lb bw should be treated with a dose of 2.3 mg/lb bw rounded up to the nearest 0.1 mL.

Administration

Shake well before use. Remove screw cap. Use the enclosed syringe for each treatment. Place the syringe nozzle firmly into the opening of the bottle. Turn the bottle upside down and withdraw the necessary volume. Turn the bottle back into an upright position before removing the syringe. The product should be administered with the syringe into the cat’s mouth. See illustrations 1 through 4 below for administration steps:

After administration, close bottle tightly with cap and store syringe in the carton together with the product. Do not disassemble or wash the syringe.

The product should be given once daily for up to 28 consecutive days. If the cat vomits after consuming any portion of the dose, the cat should not be re-dosed and should be considered as dosed for the day.

Monitoring and Repeating Treatment

Treated cats should initially have their hematocrit (HCT) or packed cell volume (PCV) levels monitored weekly beginning about the 14th day of the 28-day treatment cycle to ensure HCT or PCV does not exceed the upper limit of the reference range. Discontinue Varenzin-CA1 if HCT or PCV exceeds the upper limit of the reference range.

After treatment cessation the hematocrit level should be periodically checked (for example, weekly, every 2 weeks or monthly). When the HCT or PCV level declines below the lower limit of the reference range, a new treatment cycle should be started. The interval between treatment cycles will vary between cats and may change over time for an individual cat but should be at least 7 days.

If a cat does not respond to treatment after 3 weeks (see REASONABLE EXPECTATION OF EFFECTIVENESS), it is recommended to re-examine the animal for any other underlying condition that may contribute to anemia, such as iron deficiency, inflammatory diseases or blood loss. It is advised to treat the underlying condition before restarting treatment with Varenzin-CA1.

CONTRAINDICATIONS

Varenzin-CA1 should not be administered to cats with known hypersensitivity to molidustat or to any of the inactive ingredients.

Varenzin-CA1 should not be administered to cats that are pregnant, lactating, or intended for breeding. In an embryo-fetal-developmental toxicity study in rats, an increase incidence of ocular malformations such as flat eye rudiments and microphthalmia were observed at doses of 30 mg/kg bw per day. These effects may be due to an increase in oxygen availability, caused by molidustat-induced polycythemia. Localized hypoxia is an important factor in normal eye development. Developmental toxicity studies have not been conducted in cats. Available animal data have shown excretion of other HIF-PH inhibitors into milk. It is unknown whether molidustat is excreted into the milk of lactating cats.

WARNINGS

User Safety Warnings

Not for use in humans.

Keep this drug, including used syringes, out of reach of children. Wash hands immediately after use and/or spillage.

In case of accidental ingestion, seek medical advice immediately and show the package leaflet or the label to the physician. Symptoms of exposure to molidustat may include the following: gastrointestinal effects (nausea, vomiting, diarrhea), blood and clotting effects (increases in reticulocytes, erythropoietin, and hemoglobin), dizziness, fainting, hypertension, changes in cardiac output and cardiac index, and increases in heart rate.

Symptoms may not occur immediately; therefore, the exposed individual should be monitored. People with known hypersensitivity to molidustat sodium should avoid direct contact with this product and should administer the product with caution.

Women who are pregnant or may become pregnant should administer the product with caution. Molidustat administered orally to pregnant rats during the period of organogenesis was associated with adverse fetal outcomes (see CONTRAINDICATIONS).

Do not eat, drink, or smoke while handling this product.

Animal Safety Warnings

Keep Varenzin-CA1 in a secure location out of reach of dogs, cats, and other animals to prevent accidental ingestion or overdose.

PRECAUTIONS

Varenzin-CA1 has been associated with thromboembolic disease (see ADVERSE REACTIONS). Use with caution in cats that may be predisposed to thromboembolic disease.

Use with caution in cats with a history of seizures (see ADVERSE REACTIONS).

Phosphate binders or other products containing multivalent cations such as calcium, iron, magnesium or aluminum have been shown to chelate with other HIF-PH inhibitors. Based on information in humans, consider staggered administration of Varenzin-CA1 and phosphate binders and iron supplements (at least 1 hour apart), if possible, to prevent potentially decreasing absorption of molidustat.

Polycythemia may result from use of Varenzin-CA1. When starting Varenzin-CA1, cats should have their hematocrit (HCT) or packed cell volume (PCV) levels monitored regularly during the treatment cycle to ensure HCT or PCV does not exceed the upper limit of the reference range (see DOSAGE AND ADMINISTRATION). Clinical signs associated with polycythemia found in preapproval studies in healthy cats included changes in mucous membrane color, slightly prolonged capillary refill time, heart pounding, and tachycardia (see TARGET ANIMAL SAFETY). Polycythemia after Varenzin-CA1 administration was also associated with increases in serum potassium, creatinine, serum phosphorus, and systolic blood pressure, which were not associated with clinical signs (see ADVERSE REACTIONS and TARGET ANIMAL SAFETY).

The use of Varenzin-CA1 administered concurrently with other erythropoiesis-stimulating agents, including recombinant erythropoietin drugs, has not been studied.

The safe use of Varenzin-CA1 has not been evaluated in cats less than 1 year of age.

ADVERSE REACTIONS

The safety of Varenzin-CA1 was evaluated in a masked, controlled 28-day field study to evaluate the effectiveness of molidustat oral suspension (not commercial formulation) for the control of nonregenerative anemia associated with CKD in cats (see REASONABLE EXPECTATION OF EFFECTIVENESS). Enrollment included 21 cats; 15 cats were treated with Varenzin-CA1, and 6 cats were administered a vehicle control. Eight of these cats were subsequently enrolled in an extended open-label safety study for up to 8 additional weeks. Cats were dosed daily for 28 days. Vomiting was the most frequently reported adverse event, observed in 6/15 (40%) cats in the molidustat group and no cats in the control group. Increases in systolic blood pressure and mild transient increases in serum potassium were also observed. The most serious adverse event was a cat in the molidustat group that presented, after 28 days of treatment, in lateral recumbency with a cold front leg from a suspected thromboembolism and was euthanized.

The safety of Varenzin-CA1 was evaluated in an interim analysis of data collected in an open label safety phase of an ongoing clinical field effectiveness and safety study. Varenzin-CA1 was administered for 28 consecutive days, followed by a treatment pause of at least 7 days, then treatment was repeated for up to 4 treatment cycles. The study evaluated 55 client-owned cats with nonregenerative anemia (PCV < 28%) secondary to CKD that had received at least one dose of Varenzin-CA1 at 5 mg/kg bw in the safety phase. Cats had a mean age of 13 years (range 5.2 to 23.4) and initial body weights between 2.3 to 5.9 kilograms. At baseline just prior to enrollment into the study, 31%, 47%, and 22% of cats were in International Renal Interest Society (IRIS) Stage 2, 3, and 4 CKD, respectively (to learn more about IRIS staging, visit http://www.iris-kidney.com/index.html).

Vomiting was the most frequently reported adverse event, either alone or with other events, and was reported at least once in 29/55 (52.7%) of the cats in the study. Vomiting was more frequent on treatment days than during treatment pause.

Two cats had seizures during the study. One cat had a seizure associated with severe uremia, severe anemia, and dehydration. One cat, which had a history of a seizure about 1 year prior, had a seizure during the study and severe hypertension.

Nineteen cats died or were euthanized before completion of the safety phase of the study due to worsening CKD or declining quality of life, and one cat was euthanized due to an abdominal mass.

CONTACT INFORMATION

To report suspected adverse drug reactions, for technical assistance or to obtain a copy of the Safety Data Sheet (SDS), contact Elanco US Inc. at 1-888-545-5973.

For additional information about reporting adverse drug experiences for animal drugs, contact FDA at 1-888-FDA-VETS or http://www.fda.gov/reportanimalae.

CLINICAL PHARMACOLOGY

Mechanism of Action

Varenzin-CA1 (molidustat oral suspension) is a competitive and reversible inhibitor of hypoxia-inducible factor prolyl hydroxylase (HIF-PH). The inhibition of HIF-PH induces a dose-dependent increase of endogenous erythropoietin (EPO) by stabilizing HIF, resulting in increased erythropoiesis (red blood cell production).

Pharmacokinetics

The pharmacokinetic parameters of Varenzin-CA1 after a single oral dose of 2.5, 5, and 10 mg/kg bw and intravenous dose of 5 mg/kg bw were evaluated in a laboratory study in which 8 healthy, young adult cats (4 neutered males, 4 spayed females) received Varenzin-CA1 orally or molidustat sodium aqueous suspension intravenously, utilizing a crossover study design. Following oral administration, molidustat was rapidly absorbed.

Table 2: Mean (± standard deviation) pharmacokinetic parameters of molidustat following a single oral or intravenous dose of 5 mg/kg in cats:

Route | Oral | Intravenous
Tmax† (hour) | 1 (0.67 – 1.5) | Not Applicable
Cmax (µg/mL) | 3.86 ± 0.495 | 26.0 ± 8.42††
AUClast; (hour*µg/mL) | 13.0 ± 2.98 | 16.5 ± 2.97
AUCinf; (hour*µg/mL) | 13.1 ± 2.99 | 16.6 ± 3.01
T1/2 (hour) | 4.68 ± 0.661 | 6.28 ± 4.43
† Median and range are reported for Tmax instead of arithmetic mean and standard deviation
†† C0 back-extrapolated concentration at time 0 by a log-linear regression of first 2 data points following intravenous administration
Cmax: Maximum observed plasma concentration
Tmax: Time to maximum observed plasma concentration
AUClast: Area under the plasma concentration versus time curve from time of dosing to the last quantifiable concentration
AUCinf: Area under the plasma concentration versus time curve from time of dosing extrapolated to infinity
T1/2: Terminal elimination half-life

The pharmacokinetic parameters of molidustat after 6 daily oral doses of 5 mg/kg bw were evaluated in a second laboratory study using 8 healthy, young adult cats (4 neutered males, 4 spayed females). Minimal accumulation of molidustat in the plasma pharmacokinetic profile was observed in the study.

REASONABLE EXPECTATION OF EFFECTIVENESS

A reasonable expectation of effectiveness may be demonstrated based on evidence such as, but not limited to, pilot data in the target species or studies from published literature.

Varenzin-CA1 is conditionally approved pending a full demonstration of effectiveness.

Additional information for Conditional Approvals can be found at www.fda.gov/animalca.

A reasonable expectation of effectiveness for Varenzin-CA1 for the control of nonregenerative anemia associated with CKD in cats is supported by a 28-day, masked, randomized, controlled field study. The study was conducted at 23 U.S. and 10 European Union veterinary clinics. The study included 21 client-owned cats with nonregenerative anemia associated with CKD. The enrolled cats weighed 2 to 6 kg and ranged from 4 to 17 years of age. The enrolled cats were randomized to treatment with molidustat oral suspension (not commercial formulation) (n=15) or vehicle control (n=6). Cats were dosed based on body weight at a minimum dose of 5 mg molidustat/kg bw or an equivalent volume of vehicle control, administered orally once daily for 28 days. One molidustat-treated cat, which was dehydrated on Study Day 28, was excluded from the Study Day 28 effectiveness analysis because the dehydration may have affected the cat’s HCT results. Treatment success was based on an absolute increase of ≥4 percentage points in HCT observed on Study Day 28 compared to Study Day 0, or a relative increase of 25% in HCT on Study Day 28 compared to Study Day 0. The treatment success rate in the molidustat-treated group was numerically superior to the vehicle control group on Study Day 28 (50% [7/14] vs. 16.7% [1/6]). Eight cats from the effectiveness phase were enrolled in a continuation phase, which lasted an additional 56 days, and received, depending on their PCV, either 2.5 mg/kg or 5 mg/kg bw of the same molidustat oral suspension formulation. The continuation phase was a multi-center, unmasked, non-randomized, uncontrolled field safety and effectiveness study. During the continuation phase of the study, PCV was evaluated weekly, and HCT was evaluated on Study Days 56 and 84 (± 2 days). Treatment success for each cat during the continuation phase was defined the same as during the 28-day study. On Study Day 56, 75% (6/8) of the cats were considered successes and on Study Day 84, 62.5% (5/8) of the cats were considered successes.

TARGET ANIMAL SAFETY

The safety of Varenzin-CA1 was established in 2 laboratory studies and 2 field safety and effectiveness studies (see REASONABLE EXPECTATION OF EFFECTIVENESS for details on the first field study).

Target Animal Safety Study

In a laboratory study, molidustat oral suspension (not commercial formulation) was administered orally to healthy 10 to 11-month-old male cats (6 cats per group) at doses of 2.5 mg/kg bw or 5 mg/kg bw daily for 56 or 28 consecutive days, respectively. Cats administered 2.5 mg molidustat/kg bw were euthanized on Study Day 57, and cats administered 5 mg molidustat/kg bw were euthanized on Study Day 29. Due to HCT values over the threshold of 60%, 2 cats dosed at 2.5 mg/kg bw and 1 dosed at 5 mg/kg were euthanized on Study Day 23; another cat dosed at 5 mg/kg bw was euthanized on Study Day 25. The control group (4 cats) were untreated. No clinically relevant changes related to molidustat were observed among the cats for food consumption and body weight. The most common physical exam findings included abnormal mucous membrane color, prolongation of capillary refill time (about 3 seconds), heart pounding, and tachycardia in the molidustat oral suspension groups. Polycythemia was noted in conjunction with these exam findings (all cats had HCTs greater than 50%).

Abnormal clinical pathology findings included a mild increase in serum potassium above baseline values in the 5 mg/kg bw group and a mild increase in serum creatinine above baseline in most cats in the molidustat groups (up to 21.6% in one 5 mg/kg bw cat). At necropsy, there was an apparent dose-dependent decrease in the mean kidney to brain ratio in the molidustat groups. Numerically lower (57.17% of control) mean thymus weight was recorded in cats administered molidustat at 5 mg/kg bw. Lower thymus weights were also noted in cats administered molidustat at 2.5 mg/kg bw. The administration of molidustat was associated with histopathological findings of congestion of the vasculature in the brain, thrombosis/hemostasis in the heart, prominent myocardial vessels, minimal edematous change of valves in the heart, and acute thrombosis of large pulmonary arteries in the lung. These findings were attributed to the pharmacologic mode of action (erythropoiesis via HIF-PH inhibition) of molidustat oral suspension.

Exploratory Pharmacokinetic and Pharmacodynamic Study

Molidustat oral suspension (not commercial formulation) was administered orally to 10 male and 12 female, healthy 22 to 24-month-old cats at doses of 5 mg/kg bw (5% oily suspension, 6 cats) or 10 mg/kg bw (10% oily suspension, 5 cats; or 10% aqueous suspension, 5 cats) daily for 24, 16, or 16 consecutive days, respectively. The control group (6 cats) were administered an oily suspension vehicle-only control for 24 days. Study Day 0 was the first day of drug administration, and all cats remained on study for evaluation until Study Day 104. No clinically relevant changes related to molidustat were observed among the cats for food consumption, body weight, and physical examination. Molidustat oral suspension administration was associated with an apparent dose-related increase in vomiting. All cats in the 10 mg/kg bw groups showed a clinically relevant increase in serum creatinine on Study Day 12. One cat in the 10 mg/kg bw oily suspension group had an 86% increase in creatinine levels, which was just above the reference range, at Study Day 12. Similar increases in blood urea nitrogen were not found. All creatinine values in the 10 mg/kg bw groups returned to baseline by Study Day 97. A transient, mild increase in serum phosphorus was also noted on Study Day 12 (10 mg/kg bw groups) or Study Day 23 (5 mg/kg bw group). The increased values did not exceed the reference range for any cat and generally returned to baseline by Study Day 97. One cat in the 10 mg/kg bw oily suspension group showed a mild but clinically relevant increase in serum alanine aminotransferase (ALT) and alkaline phosphatase (ALP) levels on Study Day 12. There were no clinically relevant changes in other liver enzymes or total bilirubin. The cat also showed a concurrent 50% increase in creatinine on Study Day 12 that was at the upper end of the reference range. The rises in ALT, ALP, and creatinine on Study Day 12 values decreased by Study Day 97. There were no clinical signs related to hepatic or renal disease in this cat. The cause for the changes was not identified, but a direct drug effect or an indirect effect secondary to polycythemia could not be ruled out.

STORAGE CONDITIONS

Store at controlled room temperature 20°C – 25°C (68°F – 77°F). Excursions permitted between 15°C and 30°C (59°F – 86°F).

HOW SUPPLIED

27 mL of a 25 mg/mL oral suspension in a bottle with an oral dosing syringe.

Manufactured for:
Elanco US Inc.
Indianapolis, IN 46221 USA
Product of Germany

Varenzin-CA1, Elanco and the diagonal bar logo are trademarks of Elanco or its affiliates.

© 2025 Elanco or its affiliates

Revision date - 05/2025

PA513312X

Elanco™

Principal Display Panel – Varenzin-CA1 25 mg/mL

27 mL

Elanco™

Varenzin™-CA1
(molidustat oral suspension)

25 mg/mL

For oral use in cats only

Hypoxia-inducible factor prolyl
hydroxylase (HIF-PH) inhibitor

For the control of nonregenerative
anemia associated with
chronic kidney disease in cats

Conditionally approved by FDA pending a
full demonstration of effectiveness under
application number 141-571. It is a violation
of Federal law to use this product other
than as directed in the labeling.

CAUTION: Federal law restricts this drug to use
by or on the order of a licensed veterinarian.

27 mL

Elanco

Varenzin™-CA1
(molidustat oral suspension)

25 mg/mL

For oral use in cats only

Conditionally approved by FDA pending a full demonstration
of effectiveness under application number 141-571. It is a
violation of Federal law to use this product other than as
directed in the labeling.

CAUTION: Federal law restricts this drug to use by or on the
order of a licensed veterinarian.

Varenzin™-CA1
(molidustat oral suspension)

For oral use in cats only

90211001